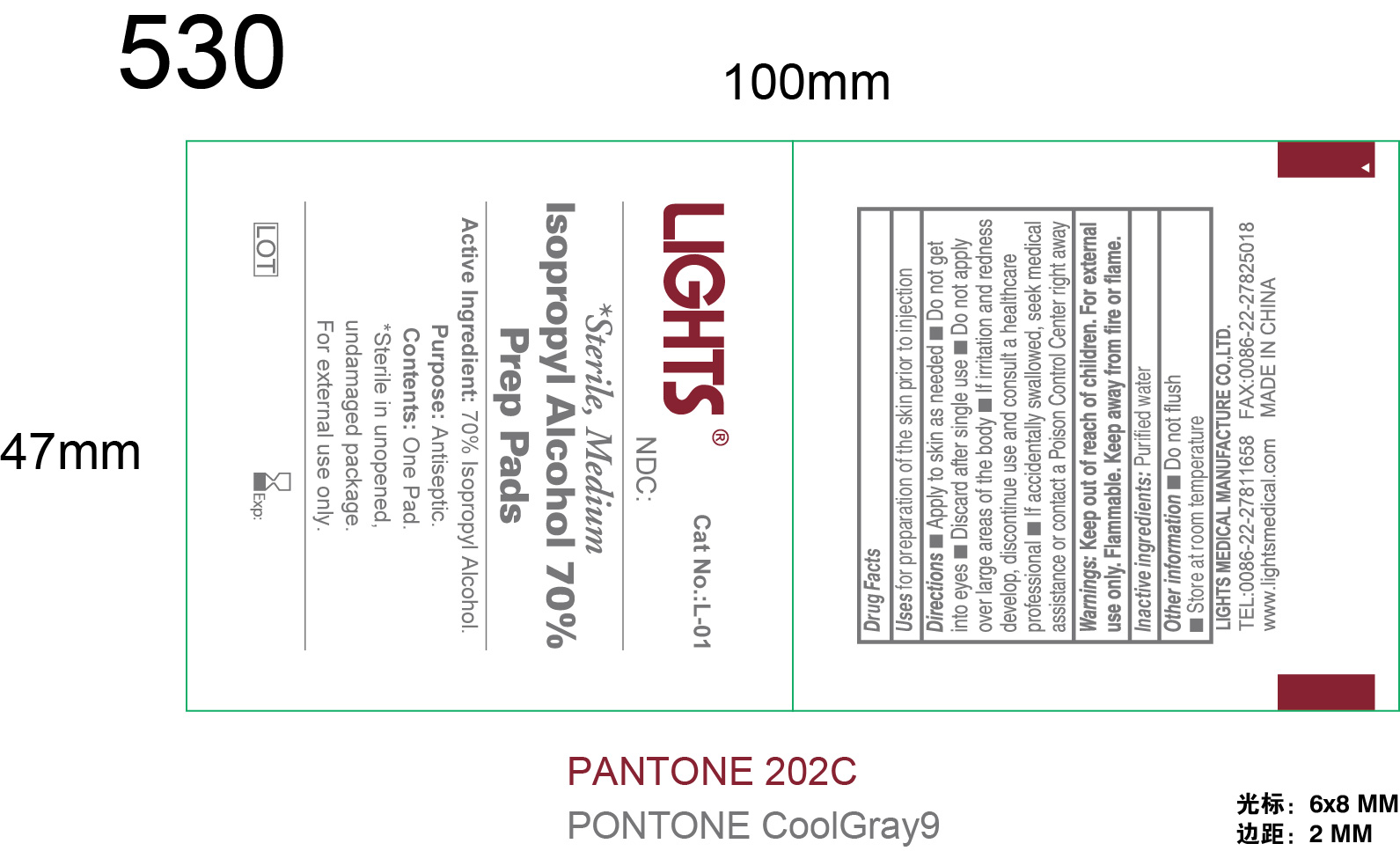 DRUG LABEL: Lights Isopropyl Alcohol Prep Pads
NDC: 61333-206 | Form: SOLUTION
Manufacturer: Lights Medical Manufacture Co., Ltd.
Category: otc | Type: HUMAN OTC DRUG LABEL
Date: 20260121

ACTIVE INGREDIENTS: ISOPROPYL ALCOHOL 70 mL/100 mL
INACTIVE INGREDIENTS: WATER

61333-206

Active Ingredient: Isopropyl Alcohol 70%

Purpose: Antiseptic

INDICATIONS AND USAGE

Uses for preparation of the skin prior to injection

Directions:

Apply to skin as needed

Do not get into eyes

Discard after single use

Do not apply over large area of the body

If irritation and redness develop, discontinue use and consult a healthcare professional

If accidentally swallowed, seek medical assistance or contact a Poison Control Center right away

Warnings:

For external use only

Flammable. Keek away from fire or flame.

Keep out of reach of children.

Other information

- Do not flush
- Store at room temperature

Inactive Ingredient

Purified Water